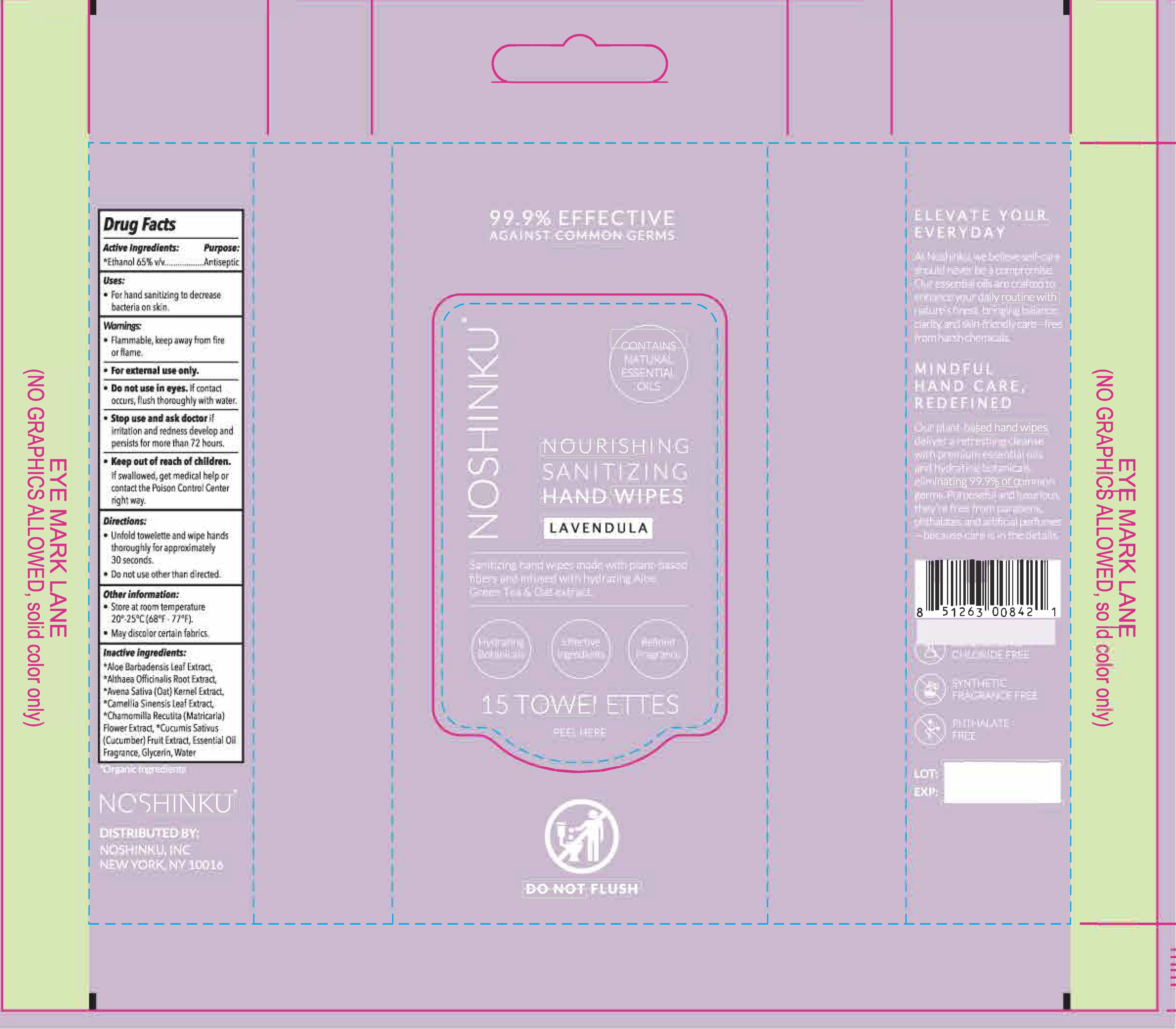 DRUG LABEL: Nourishing Sanitizing Hand Wipes
NDC: 73898-100 | Form: CLOTH
Manufacturer: Noshinku
Category: otc | Type: HUMAN OTC DRUG LABEL
Date: 20250728

ACTIVE INGREDIENTS: ALCOHOL 65 mL/100 mL
INACTIVE INGREDIENTS: GLYCERIN; CHAMOMILE; ALTHAEA OFFICINALIS ROOT; OAT; CAMELLIA SINENSIS LEAF; ALOE BARBADENSIS LEAF POWDER; WATER; CUCUMIS SATIVUS (CUCUMBER) FRUIT

Nourishing Sanitizing Hand Wipes - Lavendula 73898-100

Drug Facts

Active Ingredients

Ethanol 65% v/v

Purpose

Antiseptic

Uses

For hand sanitizing to decrease bacteria on skin.

Warnings

Flammable, keep away from fire or flame

For external use only

Do not use in eyes.

If contact occurs, flush thoroughly with water

Stop use and ask a doctor if

irritation and redness develop and persists for more than 72 hours

Keep out of reach of children.

If swallowed, get medical helps or contact the Poison Control Center right away

Directions

Unfold the towelette and wipe hands thoroughly for approximately 30 seconds
Do not use other than directed

Other Information

Store at room temperature 20°-25°C (68°F - 77°F)
May discolor certain fabrics

Inactive Ingredients

*Aloe Barbadensis Leaf Extract, *Althaea Officinalis Root Extract, *Avena Sativa (Oat) Kernel Extract, *Camellia Sinensis Leaf Extract, *Chamomilla Recutita (Matricaria) Flower Extract, *Cucumis Sativus (Cucumber) Fruit Extract, Essential Oil Fragrance, Glycerin, Water